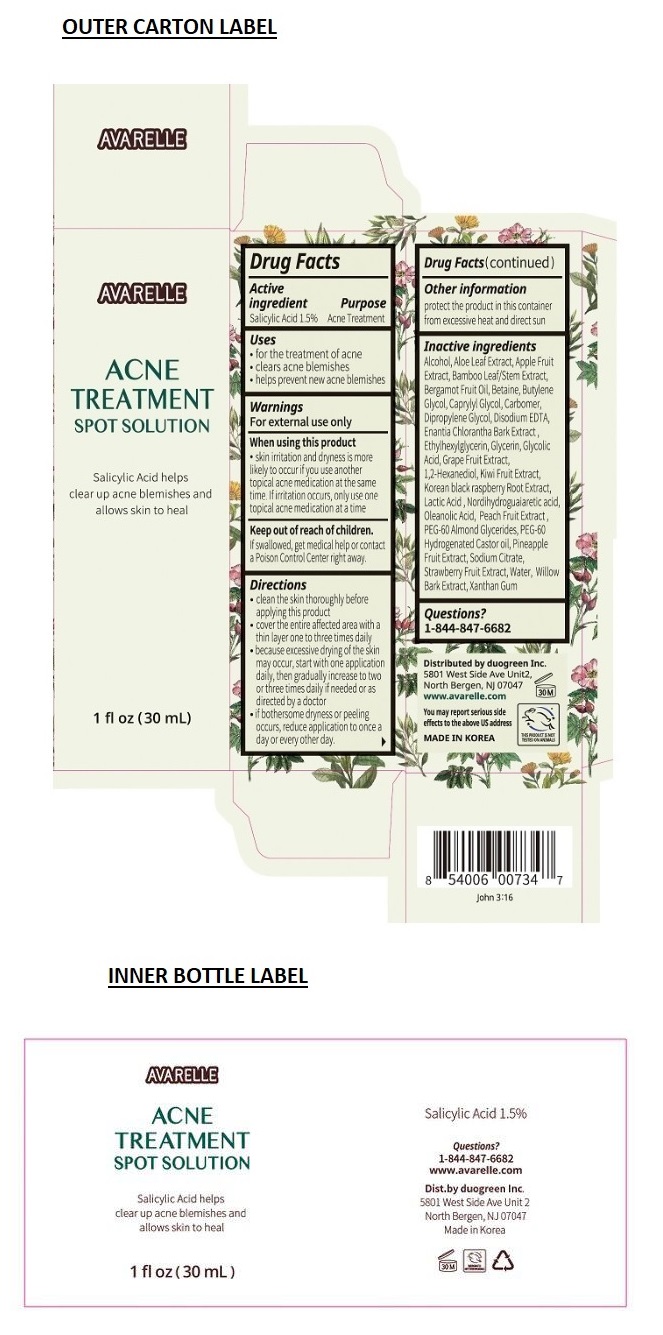 DRUG LABEL: Avarelle acne treatment spot solution
NDC: 72178-201 | Form: SOLUTION
Manufacturer: Duogreen
Category: otc | Type: HUMAN OTC DRUG LABEL
Date: 20180629

ACTIVE INGREDIENTS: SALICYLIC ACID 1.5 g/100 mL
INACTIVE INGREDIENTS: ALCOHOL; ALOE VERA LEAF; APPLE FRUIT OIL; BAMBUSA VULGARIS WHOLE; BERGAMOT OIL; BETAINE; BUTYLENE GLYCOL; CAPRYLYL GLYCOL; CARBOXYPOLYMETHYLENE; DIPROPYLENE GLYCOL; EDETATE DISODIUM ANHYDROUS; ANNICKIA CHLORANTHA BARK; ETHYLHEXYLGLYCERIN; GLYCERIN; GLYCOLIC ACID; GRAPEFRUIT; 1,2-HEXANEDIOL; KIWI FRUIT; RUBUS COREANUS FRUIT; LACTIC ACID, UNSPECIFIED FORM; MASOPROCOL; OLEANOLIC ACID; PEACH; PEG-60 ALMOND GLYCERIDES; PEG-60 HYDROGENATED CASTOR OIL; PINEAPPLE; SODIUM CITRATE, UNSPECIFIED FORM; STRAWBERRY JUICE; WATER; WILLOW BARK; XANTHAN GUM

AVARELLE ACNE TREATMENT SPOT SOLUTION

Active ingredient

Salicylic Acid 1.5%

Purpose

Acne Treatment

Uses

- for the treatment of acne

- clears acne blemishes

- helps prevent new acne blemishes

Warnings

For external use only

When using this product

- skin irritation and dryness is more likely to occur if you use another topical acne medication at the same time. If irritation occurs, only use one topical acne medication at a time

Keep out of reach of children.

If swallowed, get medical help or contact a Poison Control Center right away.

Directions

- clean the skin thoroughly before applying this product

- cover the entire affected area with a thin layer one to three times daily

- because excessive drying of the skin may occur, start with one application daily, then gradually increase to two or three times daily if needed or as directed by a doctor

- if bothersome dryness or peeling occurs, reduce application to once a day or every other day.

Inactive ingredients

Alcohol, Aloe Leaf Extract, Apple Fruit Extract, Bamboo Leaf/Stem Extract, Bergamot Fruit Oil, Betaine, Butylene Glycol, Caprylyl Glycol, Carbomer, Dipropylene Glycol, Disodium EDTA, Enantia Chlorantha Bark Extract, Ethylhexylglycerin, Glycerin, Glycolic Acid, Grape Fruit Extract, 1,2- Hexanediol, Kiwi Fruit Extract, Korean black raspberry Root Extract, Lactic Acid, Nordihydroguaiaretic acid, Oleanolic Acid, Peach Fruit Extract, PEG-60 Almond Glycerides, PEG-60 Hydrogenated Castor Oil, Pineapple Fruit Extract, Sodium Citrate, Strawberry Fruit Extract, Water, Willow Bark Extract, Xanthan Gum

Other information

protect the product in this container from excessive heat and direct sun

Questions?

1-844-847-6682

Salicylic Acid helps clear up acne blemishes and allows skin to heal

Distributed by duogreen Inc.

5801 West Side Ave Unit2,

North Bergen, NJ 07047

www.avarelle.com

You may report serious side effects to the above US address

MADE IN KOREA

THIS PRODUCT IS NOT TESTED ON ANIMALS